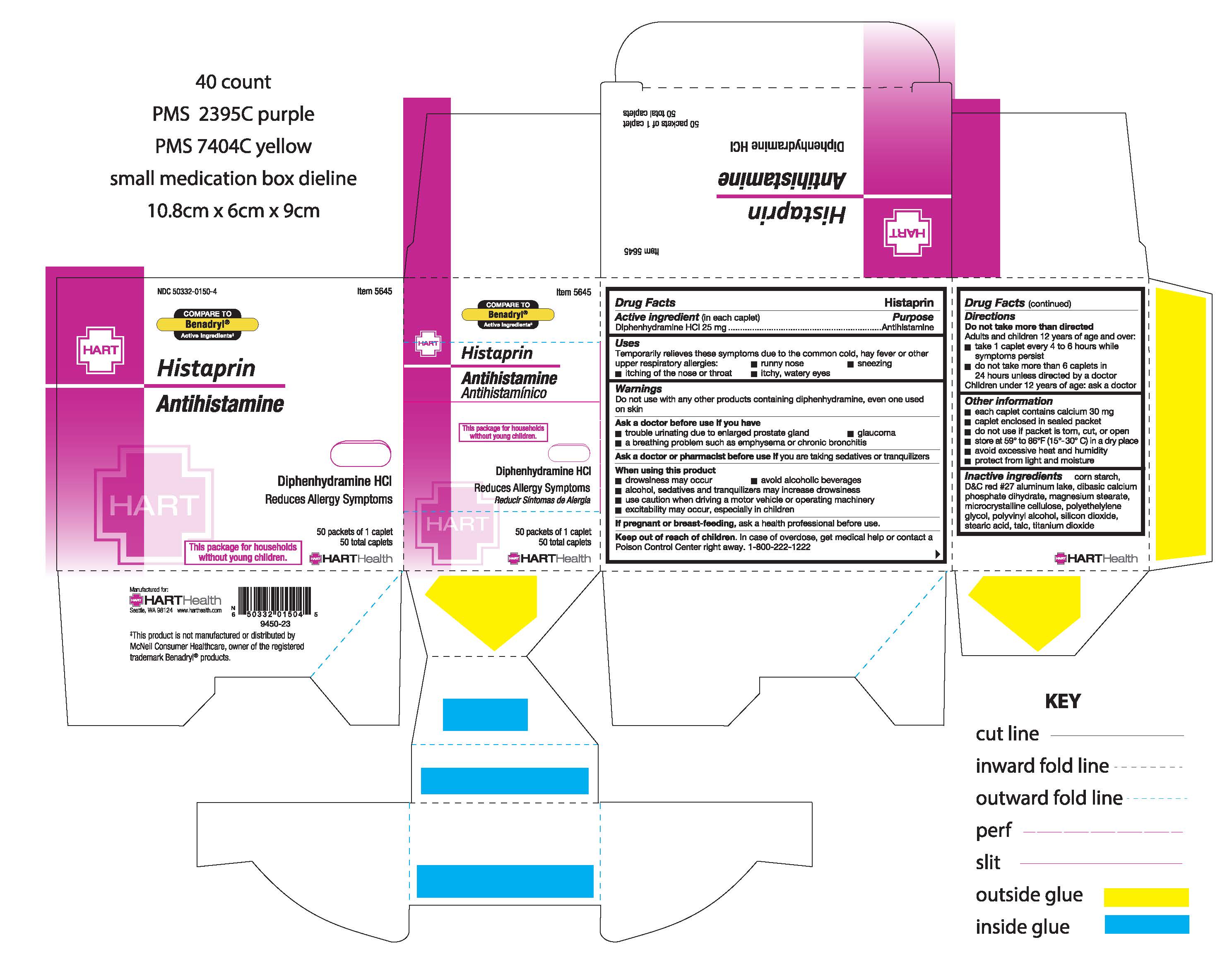 DRUG LABEL: HISTAPRIN
NDC: 50332-0150 | Form: TABLET
Manufacturer: NorMed
Category: otc | Type: HUMAN OTC DRUG LABEL
Date: 20260114

ACTIVE INGREDIENTS: DIPHENHYDRAMINE HYDROCHLORIDE 25 mg/1 1
INACTIVE INGREDIENTS: STARCH, CORN; D&C RED NO. 27 ALUMINUM LAKE; DIBASIC CALCIUM PHOSPHATE DIHYDRATE; MAGNESIUM STEARATE; CELLULOSE, MICROCRYSTALLINE; POLYETHYLENE GLYCOL, UNSPECIFIED; POLYVINYL ALCOHOL, UNSPECIFIED; SILICON DIOXIDE; STEARIC ACID; TALC; TITANIUM DIOXIDE

HISTAPRIN

Active Ingredient (in each caplet)

Diphenhydramine Hydrochloride 25mg

Purpose:

Antihistamine

Uses:

Temporarily relieves these symptoms due to the common cold, hay fever, or other upper respiratory allergies:

- runny nose
- sneezing
- itching of the nose or throat
- itchy, watery eyes

Warnings:

Do not use with any other products containing diphenhydramine, even one used on skin

Ask a doctor before use if you have:

- trouble urinating due to enlarged prostate gland
- glaucoma
- a breathing problem such as emphysema or chronic bronchitis

Ask a doctor or pharmacist before use if you are taking sedatives or tranquilizers

When using this product:

- drowsiness may occur
- avoid alcoholic beverages
- alcohol, sedatives and tranquilizers may increase the drowsiness effect
- use caution when driving a motor vehicle or operating machinery
- excitability may occur, especially in children

PREGNANCY OR BREAST FEEDING

If pregnant or breast-feeding, ask a health professional before use.

Keep out of reach of children. In case of overdose, get medical help or contact a Poison Control Center right away. 1-800-222-1222

Directions

Do not take more than directed

Adults and children 12 years of age and over:

- Take 1 caplet every 4 to 6 hours while symptoms persist
- do not take more than 6 caplets in 24 hours unless directed by a doctor

Children under 12 years of age: ask a doctor

Other information:

- each caplet contains calcium 30mg
- caplet enclosed in a sealed packet
- do not use if packet is torn, cut, or open
- store at 59° to 86°F (15°-30°C) in a dry place
- avoid excessive heat and humidity
- protect from light and moisture

INACTIVE INGREDIENT

corn starch, D&C red #27 aluminum lake, dibasic calcium phosphate dihydrate, magnesium stearate, microcrystalline cellulose, polyethylene glycol, polyvinyl alcohol, silicon dioxide, stearic acid, talc, titanium dioxide